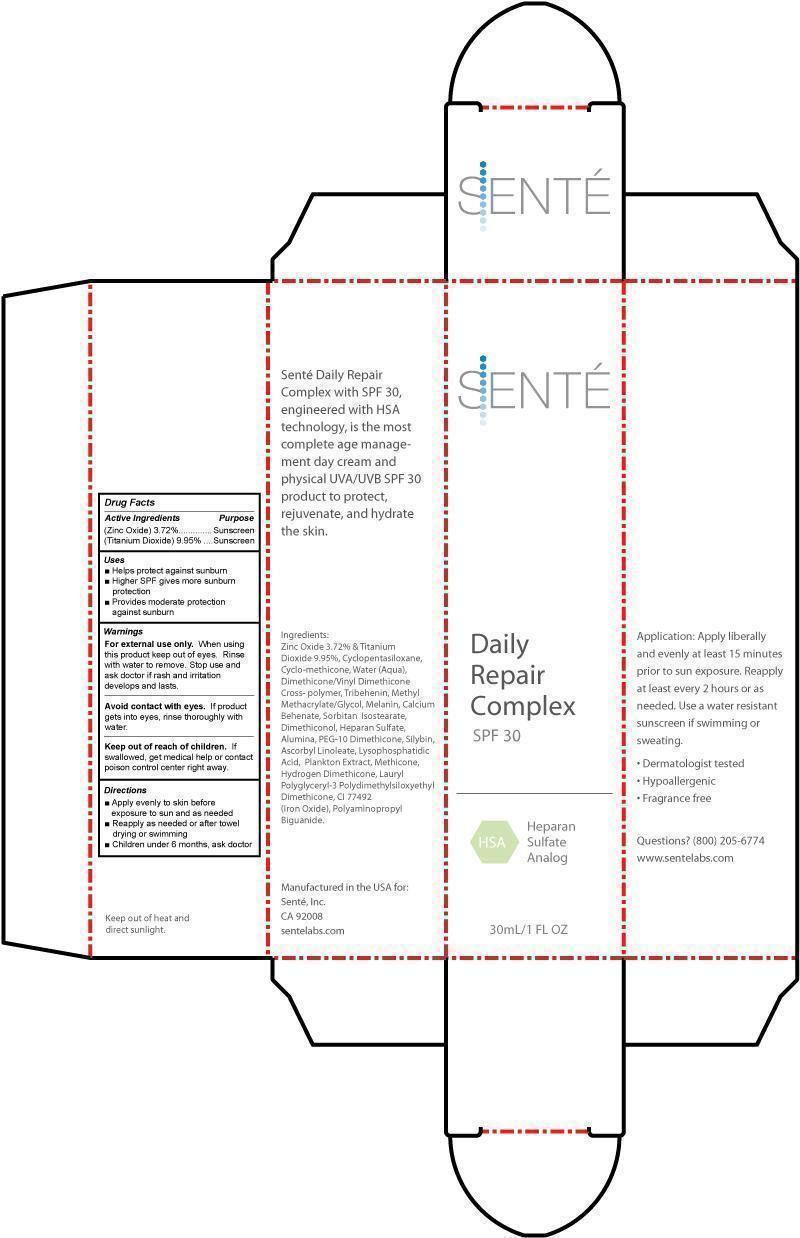 DRUG LABEL: Sente Daily Repair Complex
NDC: 59958-220 | Form: CREAM
Manufacturer: Owen Biosciences, Inc.
Category: otc | Type: HUMAN OTC DRUG LABEL
Date: 20241105

ACTIVE INGREDIENTS: TITANIUM DIOXIDE 9.95 g/100 g; ZINC OXIDE 3.72 g/100 g
INACTIVE INGREDIENTS: TRIBEHENIN 1.25 g/100 g; DIMETHICONE/VINYL DIMETHICONE CROSSPOLYMER (SOFT PARTICLE) 4.68 g/100 g; WATER 7 g/100 g; CALCIUM BEHENATE 1.25 g/100 g; MELANIN SYNTHETIC (TYROSINE, PEROXIDE) 1.5 g/100 g; SORBITAN ISOSTEARATE 1.5 g/100 g; PEG-10 DIMETHICONE (600 CST) 0.5 g/100 g; METHICONE (20 CST) 0.5 g/100 g; DIMETHICONE CROSSPOLYMER (450000 MPA.S AT 12% IN CYCLOPENTASILOXANE) 43 g/100 g; METHYL METHACRYLATE/GLYCOL DIMETHACRYLATE CROSSPOLYMER 2 g/100 g; FERRIC OXIDE RED 0.116 g/100 g; FERRIC OXIDE YELLOW 0.116 g/100 g

Sente Daily Repair Complex

Drug Facts

Active ingredients Purpose

(Zinc Oxide) 3.72% Sunscreen

(Titanium Dioxide) 9.95% Sunscreen

USES

Helps protect against sunburn

Higher SPF gives more sunburn protection

Provides moderate protection against sunburn.

WARNINGS

For external use only. When using this product keep
out of eyes. Rinse with water to remove. Stop use and
ask doctor if rash and irritation develops and lasts.

Avoid contact with eyes. If product gets into eyes,
rinse thoroughly with water.

Keep out of reach of children. If swallowed, get
medical help or contact poison control center right
away.

Keep out of reach of children. If swallowed, get medical help or contact poison control center right away.

Directions

Apply evenly to skin before exposure to sun and as needed.

Reapply as needed or after towel drying or swimming.

For children under 6 months, ask a doctor.

Inactive Ingredients

Cyclopentasiloxane, Cyclo-methicone, Water (Aqua), Dimethicone/Vinyl Dimethicone Cross-polymer, Melanin, Tribehenin, Methyl Methacrylate/Glycol, Calcium Behenate, Sorbitan Isostearate, Dimethiconol, Heparan Sulfate, Alumina, PEG-10 Dimethicone, Silybin, Ascobyl Linoleate, Lysophosphatidic Acid, Plankton Extract, Methicone, hydrogen Dimethicone, Lauryl Polyglyceryl-3 Polydimethylsiloxyethyl Dimethicone, CI 77492 (Iron Oxide), Polyaminopropyl Biguanide

Dosage & Administration

Directions

- Apply enenly to skin before exposure to sun and as needed

- Reapply as needed or after towel drying or swimming

- Children under 6 months, ask doctor